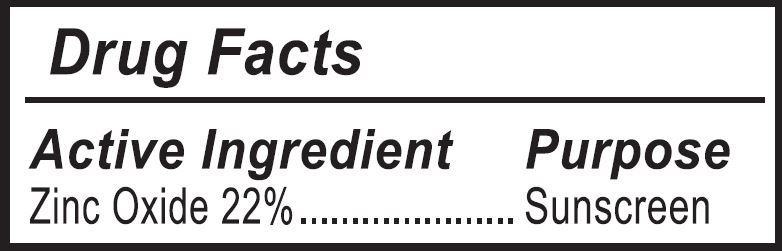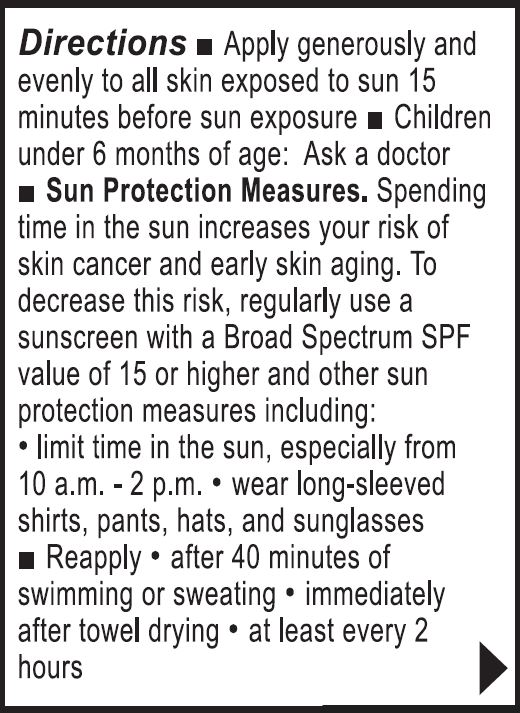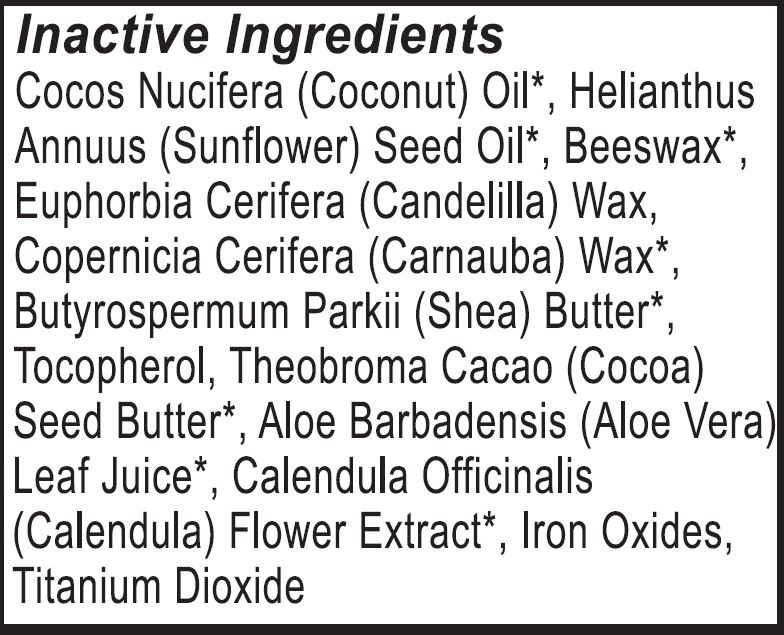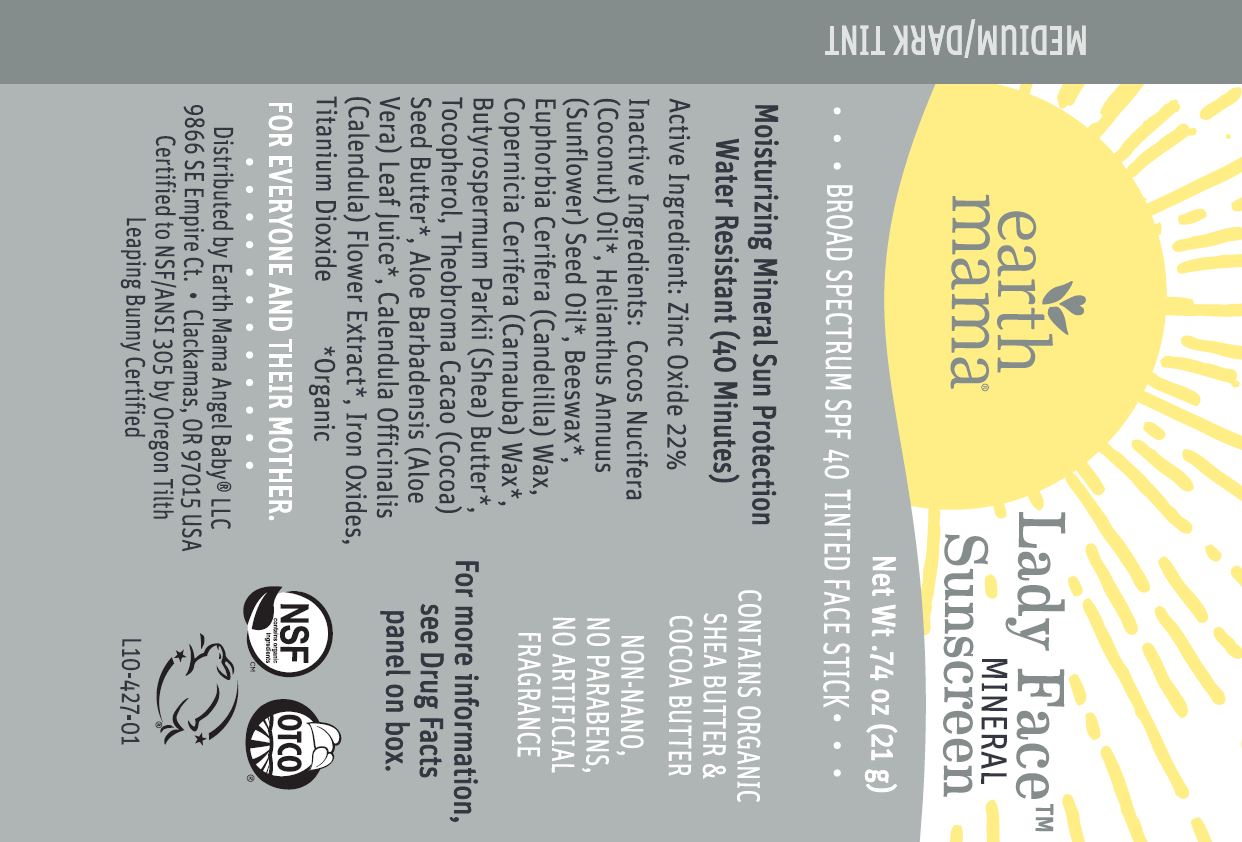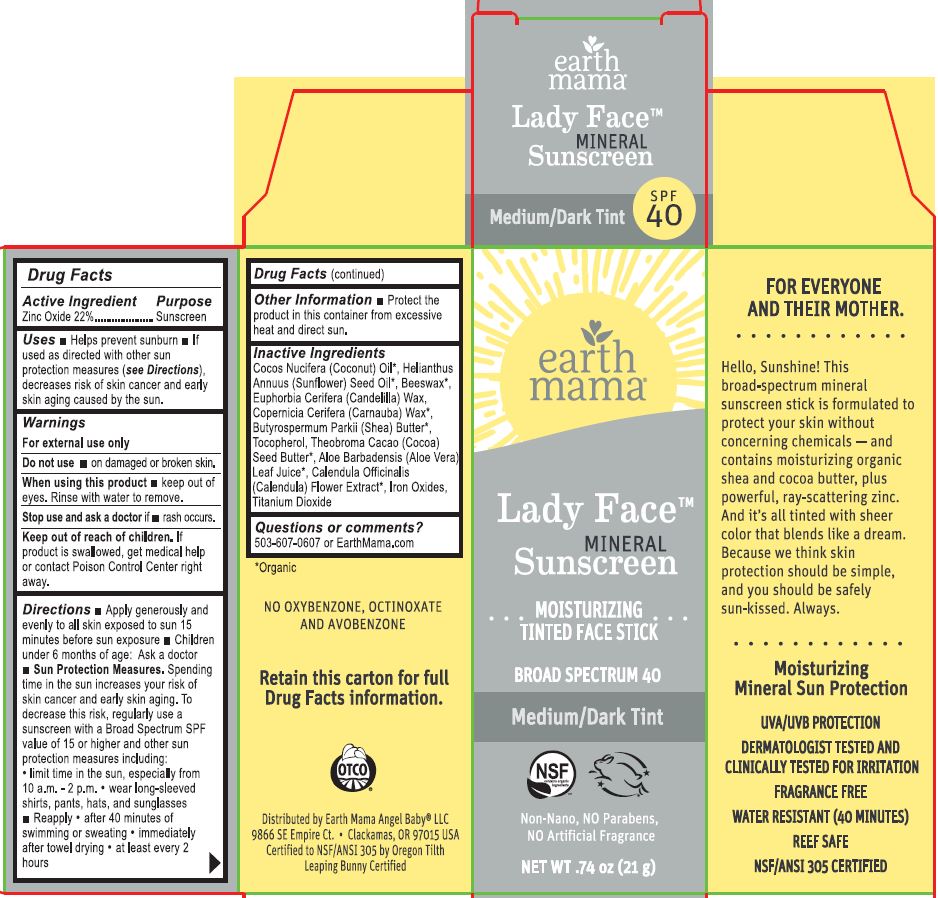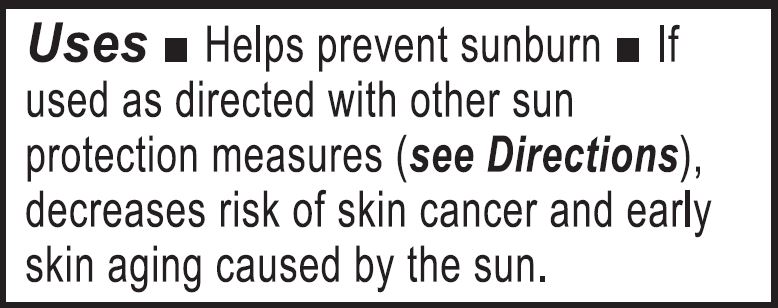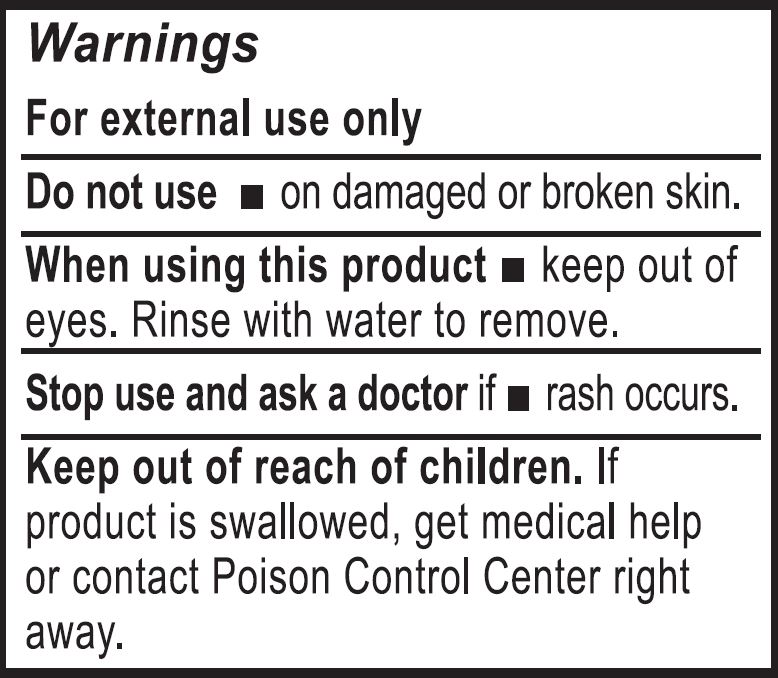 DRUG LABEL: Lady Face Mineral Sunscreen, SPF 40 - Medium/Dark
NDC: 62932-258 | Form: STICK
Manufacturer: Private Label Select Ltd CO
Category: otc | Type: HUMAN OTC DRUG LABEL
Date: 20210101

ACTIVE INGREDIENTS: ZINC OXIDE 20 g/100 g
INACTIVE INGREDIENTS: .GAMMA.-TOCOPHEROL; FERRIC OXYHYDROXIDE; .ALPHA.-TOCOPHEROL, D-; .DELTA.-TOCOPHEROL; FERRIC OXIDE YELLOW; COCOA BUTTER; .BETA.-TOCOPHEROL; COCONUT OIL; WHITE WAX; CANDELILLA WAX; CARNAUBA WAX; SUNFLOWER OIL; SHEA BUTTER; ALOE VERA LEAF; CALENDULA OFFICINALIS FLOWER

Earth Mama Lady Face Mineral Sunscreen, SPF 40 - Medium/Dark